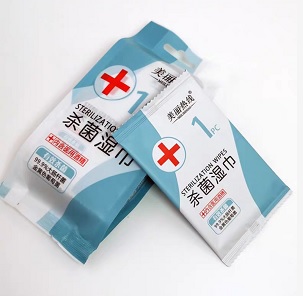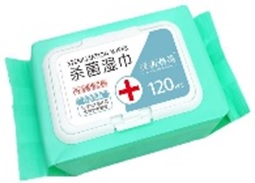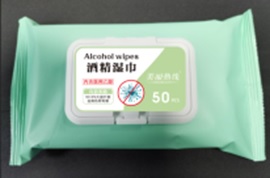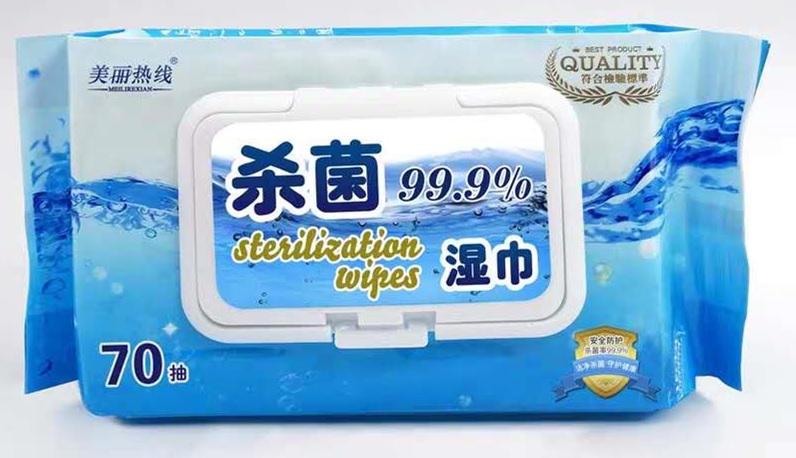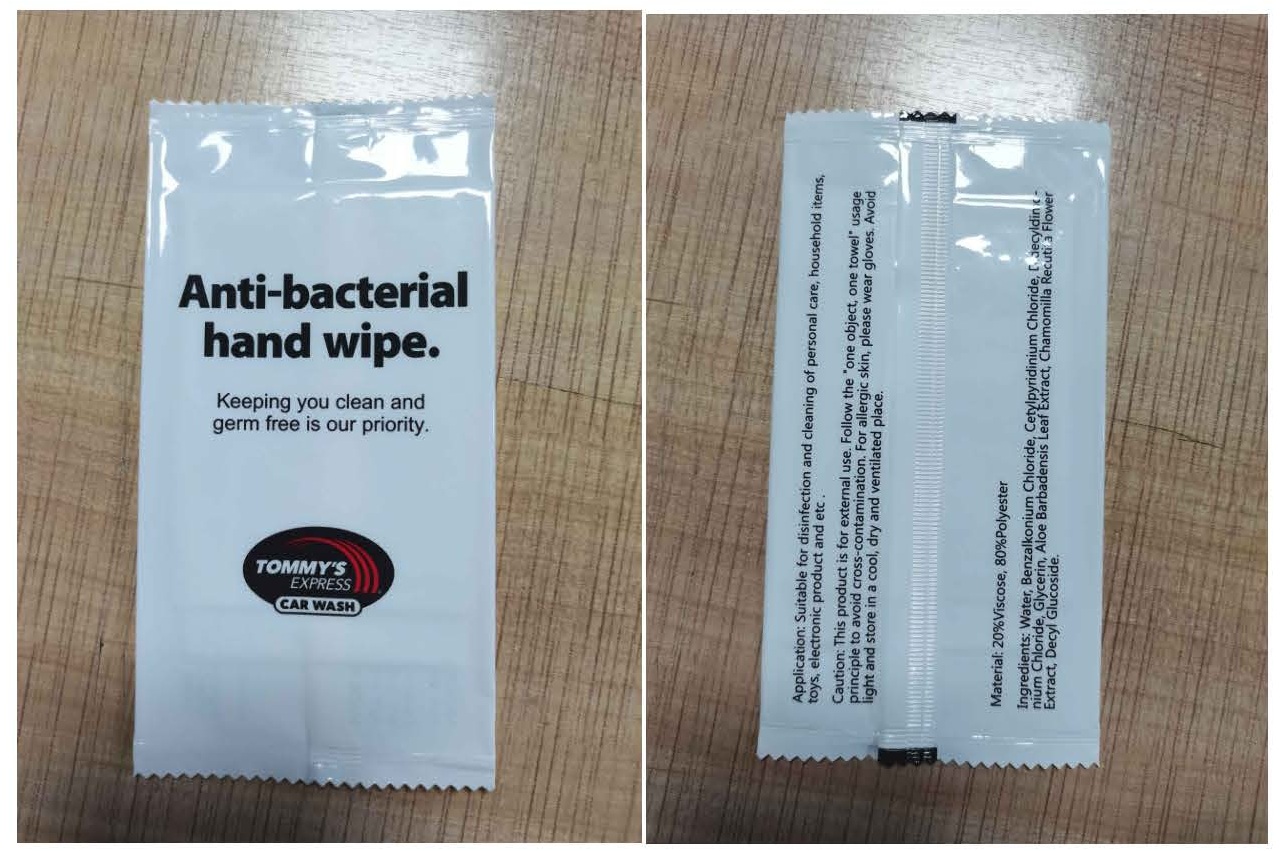 DRUG LABEL: Disinfectant wet wipe
NDC: 75111-301 | Form: CLOTH
Manufacturer: Enping Jiaxin Daily Necessities Co., Ltd.
Category: otc | Type: HUMAN OTC DRUG LABEL
Date: 20220128

ACTIVE INGREDIENTS: CETYLPYRIDINIUM CHLORIDE 0.5 mg/1 mL; BENZALKONIUM CHLORIDE 0.8 mg/1 mL; DIDECYLDIMONIUM CHLORIDE 0.32 mg/1 mL
INACTIVE INGREDIENTS: WATER; DECYL GLUCOSIDE; ALOE VERA LEAF; GLYCERIN; CHAMOMILE FLOWER OIL

Disinfectant wet wipe

Disinfectant wet wipe

Active Ingredient(s)

Benzalkonium chloride 0.8mg/mL
Cetylpyridinium Chloride 0.5mg/mL
Didecyldimonium Chloride 0.32mg/mL

Purpose: Antiseptic

Purpose

Antiseptic

Use

Disinfectant wet wipe to help reduce bacteria that potentially can cause disease. For use when soap and water are not available.

Warnings

For external use only. Flammable. Keep away from heat or flame

Do not use

- in children less than 2 months of age
- on open skin wounds

When using this product keep out of eyes, ears, and mouth. In case of contact with eyes, rinse eyes thoroughly with water.
Stop use and ask a doctor if irritation or rash occurs. These may be signs of a serious condition.
Keep out of reach of children. If swallowed, get medical help or contact a Poison Control Center right away.

Stop use and ask a doctor if irritation or rash occurs. These may be signs of a serious condition.

Keep out of reach of children. If swallowed, get medical help or contact a Poison Control Center right away.

Directions

- Wipe the body skin or other surface
- Supervise children under 6 years of age when using this product to avoid swallowing.

Other information

- Store between 15-30C (59-86F)
- Avoid freezing and excessive heat above 40C (104F)

Inactive ingredients

Glycerin
Aloe Barbadensis Leaf Extract
Chamomilla Recutita Flower Extract
Decyl glucoside
Aqua